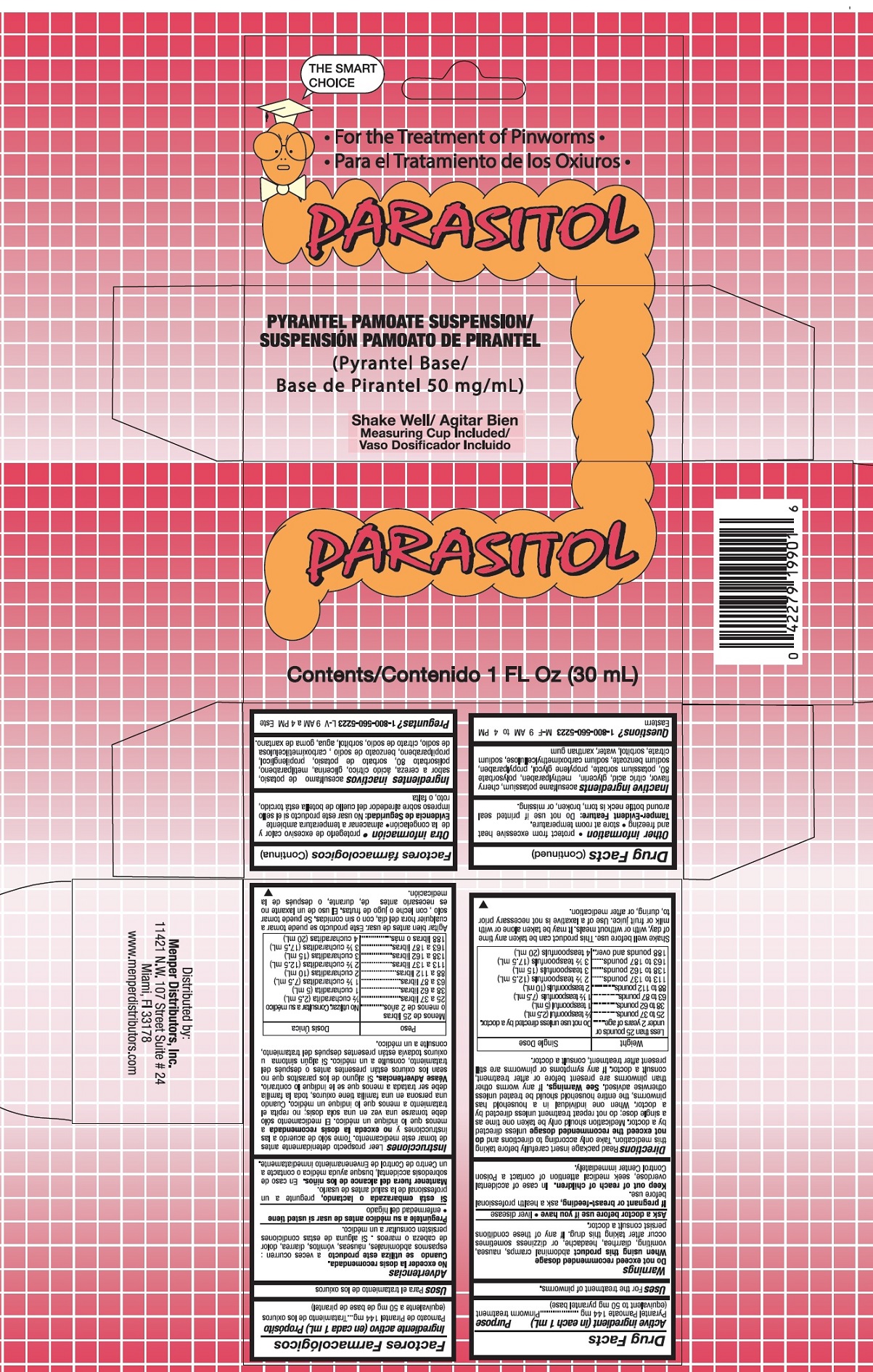 DRUG LABEL: PARASITOL
NDC: 53145-101 | Form: SUSPENSION
Manufacturer: Menper Distributors Inc.
Category: otc | Type: HUMAN OTC DRUG LABEL
Date: 20250722

ACTIVE INGREDIENTS: PYRANTEL PAMOATE 144 mg/1 mL
INACTIVE INGREDIENTS: ACESULFAME POTASSIUM; ANHYDROUS CITRIC ACID; GLYCERIN; METHYLPARABEN; POLYSORBATE 80; POTASSIUM SORBATE; PROPYLENE GLYCOL; PROPYLPARABEN; SODIUM BENZOATE; CARBOXYMETHYLCELLULOSE SODIUM; SODIUM CITRATE; SORBITOL; WATER; XANTHAN GUM

PARASITOL

ACTIVE INGREDIENTS

PYRANTEL PAMOATE 144 MG (equivalent to 50 mg pyrantel base)

PURPOSE

Pinworm treatment

USES

FOR THE TREATMENT OF PINWORMS.

WARNINGS

Do not Exceed recommended usage

Whenm using this product abdominal cramps, nausea, vomiting, diarrhea, headache, or dizziness sometimes occur after taking this drug. If any of these conditions persist consult a doctor.

Ask a doctor before use if you have liver disease

PREGNANCY OR BREAST FEEDING

If pregnant or breast-feeding, ask a health professional before use.

KEEP OUT OF REACH OF CHILDREN. In case of accidental overdose, seek medical attention or contact a Poison Control Center Immediately.

Directions

Read package insert carefully before taking this medication. Take only according to directions and do not exceed the recommended dosage unless direct by a doctor. Medication should only be taken one time as a single dose; do not repeat treatment unless direct by a doctor. When one individual in a household has pinworms, the entire household should be treated unless otherwise advised. See Warnings. If any worms other than pinworms are present before or after treatmen, consult a doctor. If any symptoms or pinworms are still present after treatment, consult a doctor.

Weight | Single Dose
Less than 25 pounds or under 2 years of age | Do not use unless directed by a doctor
25 to 37 pounds | 1/2 teaspoonful (2.5 mL)
38 to 62 pounds | 1 teaspoonful (5 mL)
63 to 87 pounds | 1 1/2 teaspoonfuls (7.5 mL)
88 to 112 pounds | 2 teaspoonfuls (10 mL)
113 to 137 pounds | 2 1/2 teaspoonfuls (12.5 mL)
138 to 162 pounds | 3 teaspoonfuls (15 mL)
163 to 187 pounds | 3 1/2 teaspoonfuls (17.5 mL)
188 pounds and over | 4 teaspoonfuls (20 mL)

Shake well before use. This product can be taken any time of day, with or without meals. It may be taken alone or with milk or fruit juice. Use of a laxative is not necessary prior to, during, or after medication.

INACTIVE INGREDIENTS

acesulfame potassium, cherry flavor, citric acid, glycerin, methylparaben, polysorbate 80, potassium sorbate, propylene glycol, propylparaben, sodium bezoate, sodium carboximethylcellulose, sodium citrate, sorbitol, water, xanthan gum